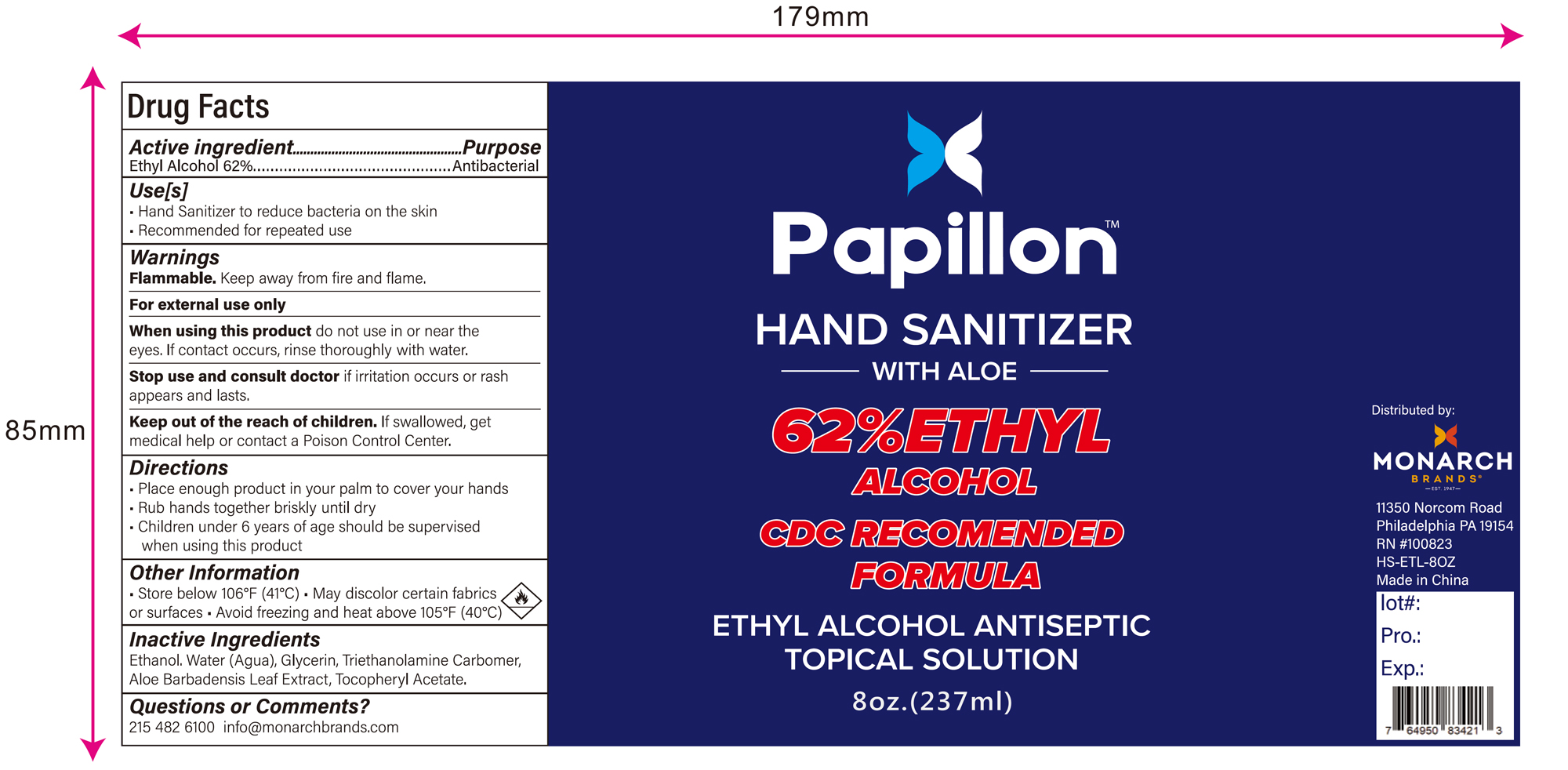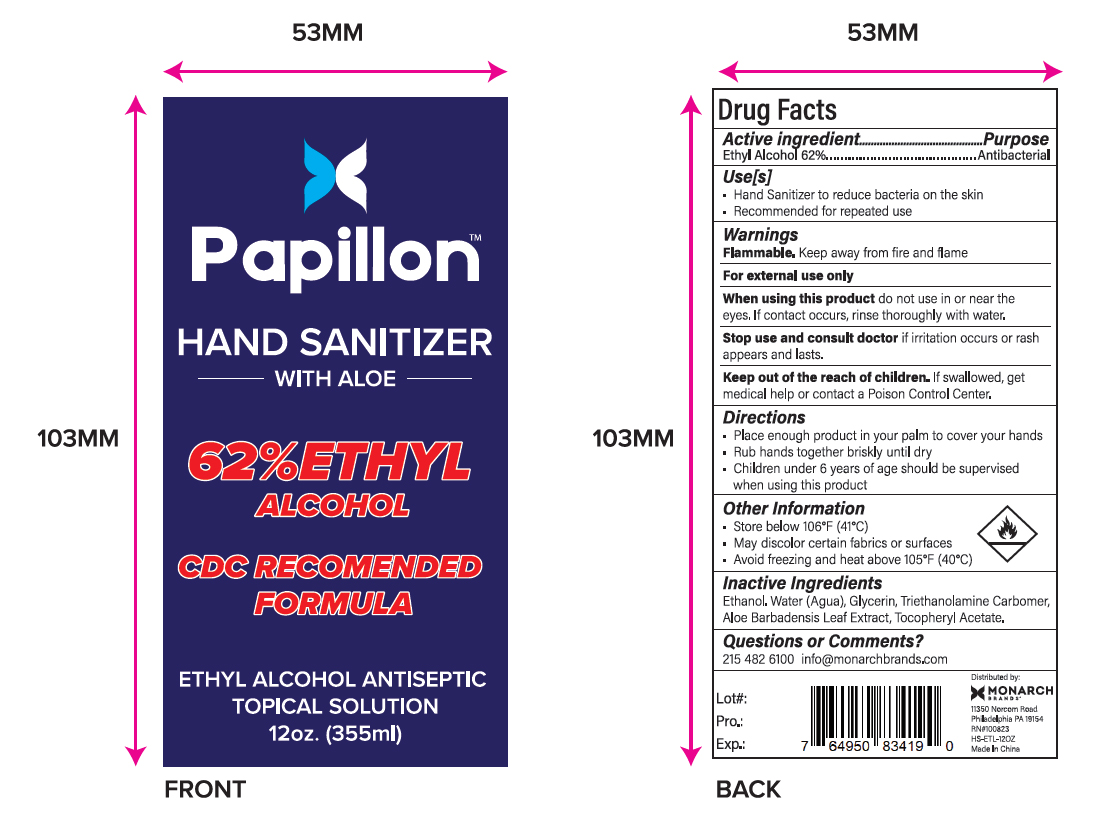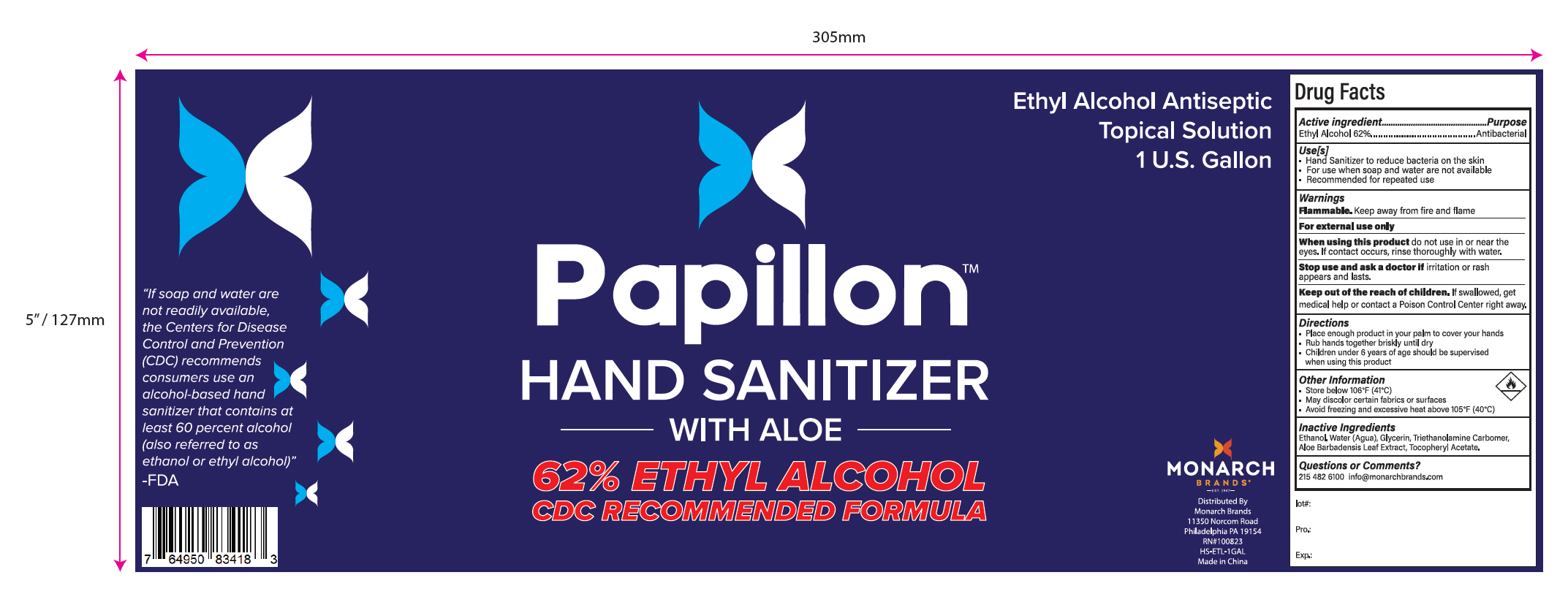 DRUG LABEL: Hand Sanitizer
NDC: 80330-001 | Form: GEL
Manufacturer: Monarch Global Brands, Inc.
Category: otc | Type: HUMAN OTC DRUG LABEL
Date: 20200827

ACTIVE INGREDIENTS: ALCOHOL 62 mL/100 mL
INACTIVE INGREDIENTS: ALOE VERA LEAF; ALPHA-TOCOPHEROL ACETATE; CARBOMER HOMOPOLYMER, UNSPECIFIED TYPE; TROLAMINE; WATER; GLYCERIN

Hand Sanitizer

Active Ingredient

Ethyl Alcohol 62% v/v. Purpose: Antibacterial

Purpose

Antibacterial, Hand Sanitizer

Use[s]

- Hand Sanitizer to reduce bacteria on the skin
- Recommended for repeated use

Warnings

Flammable., keep away from fire and flame

For external use only

When using this product

do not use in or near the eyes. If contact occurs, rinse thoroughly with water.

Stop use and consult doctor

if irritation occurs or rash appears and lasts.

Keep out of reach of Children.

If swallowed, get medical help or call a Poison Control Center.

Directions

- Place enough product in your palm to cover your hands
- Rub hands together briskly until dry
- Children under 6 years of age should be supervised when using this product

Other information

- Store below 106F (41C)
- May discolor certain fabrics or surfaces
- Avoid freezing and heat above 105F (40C)

Inactive ingredients

water, glycerin，triethanolamine,carbomer, Aloe Barbadensis Leaf extract, Tocopheryl Acetate

Questions or Comments?

215 482 6100

info@monarchbrands.com

Package Label - Principal Display Panel

237mL NDC: 80330-007-01

Papillon

HAND SANITIZER

WITH ALOE

62% ETHYL

ALCOHOL

CDC RECOMENDED

FORMULA

ETHYL ALCOHOL ANTISEPTIC

TOPICAL SOLUTION

8 oz. (237ml)

355mL NDC: 80330-007-02

Papillon

HAND SANITIZER

WITH ALOE

62% ETHYL

ALCOHOL

CDC RECOMENDED

FORMULA

ETHYL ALCOHOL ANTISEPTIC

TOPICAL SOLUTION

12 oz. (355ml)

3785mL NDC: 80330-007-03

Papillon

HAND SANITIZER

WITH ALOE

62% ETHYL

ALCOHOL

CDC RECOMENDED

FORMULA

ETHYL ALCOHOL ANTISEPTIC

TOPICAL SOLUTION

1 U.S. Gallon